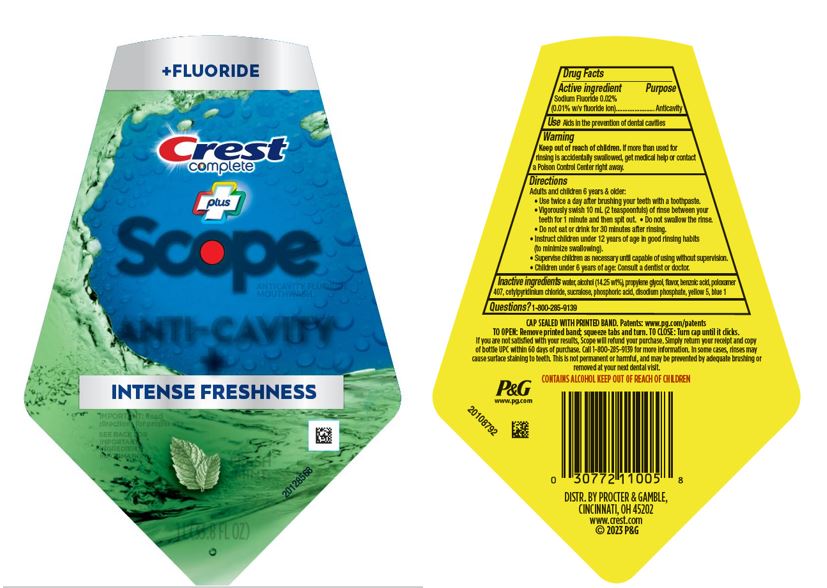 DRUG LABEL: Crest Complete Plus Scope
NDC: 69423-709 | Form: RINSE
Manufacturer: The Procter & Gamble Manufacturing Company
Category: otc | Type: HUMAN OTC DRUG LABEL
Date: 20250114

ACTIVE INGREDIENTS: SODIUM FLUORIDE 1 g/1 mL
INACTIVE INGREDIENTS: ALCOHOL; PROPYLENE GLYCOL; POLOXAMER 407; WATER; FD&C YELLOW NO. 5; BENZOIC ACID; PHOSPHORIC ACID; CETYLPYRIDINIUM CHLORIDE; SODIUM PHOSPHATE, DIBASIC, ANHYDROUS; SUCRALOSE

Crest complete Plus Scope Intense Freshness Rinse

Drug Facts

Active ingredient

Sodium Fluoride 0.02%
(0.01% w/v fluoride ion)

Purpose

Anticavity

Uses

Aids in the prevention of dental cavities

Warnings

Keep out of reach of children. If more than used for
rinsing is accidentally swallowed, get medical help or contact
a Poison Control Center right away.

Directions

- Adults and children 6 years & older:
  • Use twice a day after brushing your teeth with a toothpaste.
  • Vigorously swish 10 mL (2 teaspoonfuls) of rinse between your
  teeth for 1 minute and then spit out. • Do not swallow the rinse.
  • Do not eat or drink for 30 minutes after rinsing.
  • Instruct children under 12 years of age in good rinsing habits
  (to minimize swallowing).
  • Supervise children as necessary until capable of using without supervision.
  • Children under 6 years of age: Consult a dentist or doctor.

Inactive ingredients

water, alcohol (14.25 wt%), propylene glycol, flavor, benzoic acid, poloxamer
407, cetylpyridinium chloride, sucralose, phosphoric acid, disodium phosphate, yellow 5, blue 1

Questions?

1–800–285–9139

PRINCIPAL DISPLAY PANEL - 1000 mL Bottle Label

+FLUORIDE

Crest

complete

plus Scope

ANTICAVITY FLUORIDE

MOUTHWASH

ANTI-CAVITY

+

INTENSE FRESHNESS

IMPORTANT: Read

directions for proper use.

SEE BACK FOR

IMPORTANT

INGREDIENT

INFORMATION

FRESH MINT

1L (33.8 FL OZ)